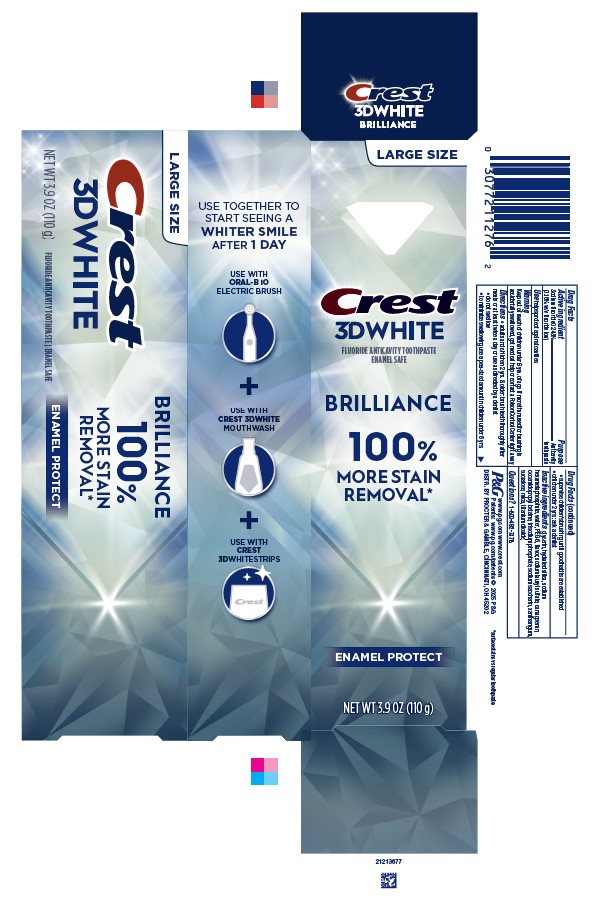 DRUG LABEL: Crest 3D White Brilliance
NDC: 69423-750 | Form: PASTE, DENTIFRICE
Manufacturer: The Procter & Gamble Manufacturing Company
Category: otc | Type: HUMAN OTC DRUG LABEL
Date: 20260108

ACTIVE INGREDIENTS: SODIUM FLUORIDE 1.6 mg/1 g
INACTIVE INGREDIENTS: GLYCERIN; TITANIUM DIOXIDE; CARRAGEENAN; SODIUM POLYMETAPHOSPHATE; SODIUM PHOSPHATE, TRIBASIC, ANHYDROUS; POLYETHYLENE GLYCOL 300; WATER; HYDRATED SILICA; COCAMIDOPROPYL BETAINE; SACCHARIN SODIUM; SODIUM LAURYL SULFATE; XANTHAN GUM; SUCRALOSE; MICA

Crest 3D White Brilliance Pro Enamel Protect

Drug Facts

Active ingredient

Sodium fluoride 0.243% (0.16% w/v fluoride ion)

Purpose

Anticavity toothpaste

Use

helps protect against cavities

Warning

Keep out of reach of children under 6 yrs. of age. If more than used for brushing is accidentally swallowed, get medical help or contact a Poison Control Center right away.

Directions

- adults and children 2 yrs. & older: brush teeth thoroughly after meals or at least twice a day or use as directed by a dentist
  - do not swallow
  - to minimize swallowing use a pea-sized amount in children under 6
  - supervise children's brushing until good habits are established
- children under 2 yrs.: ask a dentist

Inactive ingredients

glycerin, hydrated silica, sodium hexametaphosphate, water, PEG-6, flavor, sodium lauryl sulfate, carrageenan, cocamidopropyl betaine, trisodium phosphate, sodium saccharin, xanthan gum, sucralose, mica, titanium dioxide

Questions?

1-800-492-7378

Dist. by Procter & Gamble,
Cincinnati, OH 45202

PRINCIPAL DISPLAY PANEL - 110 g Tube Carton

LARGE SIZE

CREST

3D WHITE

fluoride anticavity toothpaste

enamel safe

BRILLIANCE

100%

MORE STAIN

REMOVAL*

ENAMEL PROTECT

NT WT 3.9 OZ (110 g)